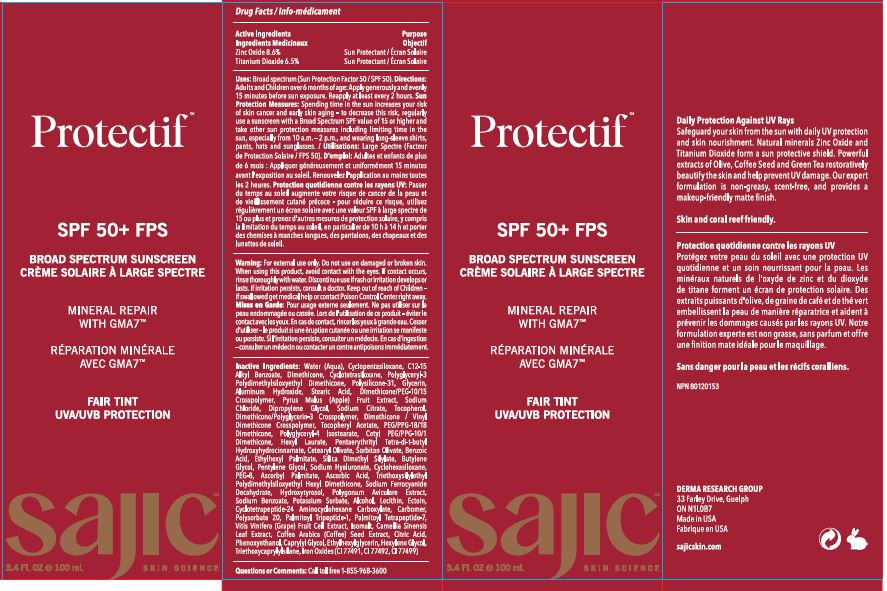 DRUG LABEL: Protectif Fair Tint
NDC: 82038-006 | Form: CREAM
Manufacturer: Derma Research Group Inc.
Category: otc | Type: HUMAN OTC DRUG LABEL
Date: 20240618

ACTIVE INGREDIENTS: ZINC OXIDE 8.6 g/100 g; TITANIUM DIOXIDE 6.5 g/100 g
INACTIVE INGREDIENTS: GLYCERIN; POLYGLYCERYL-4 ISOSTEARATE; PENTAERYTHRITOL TETRAKIS(3-(3,5-DI-TERT-BUTYL-4-HYDROXYPHENYL)PROPIONATE); FERRIC OXIDE RED; TRIETHOXYCAPRYLYLSILANE; WATER; PENTYLENE GLYCOL; PALMITOYL TRIPEPTIDE-1; DIMETHICONE/VINYL DIMETHICONE CROSSPOLYMER (SOFT PARTICLE); HEXYL LAURATE; CETEARYL OLIVATE; CYCLOMETHICONE 5; .ALPHA.-TOCOPHEROL ACETATE; HEXYLENE GLYCOL; FERROSOFERRIC OXIDE; POTASSIUM SORBATE; DIMETHICONE; SILICA DIMETHYL SILYLATE; FERRIC OXIDE YELLOW; SODIUM FERROCYANIDE DECAHYDRATE; PHENOXYETHANOL; APPLE; SODIUM CHLORIDE; TOCOPHEROL; ALKYL (C12-15) BENZOATE; POLYGLYCERYL-3 POLYDIMETHYLSILOXYETHYL DIMETHICONE (4000 MPA.S); DIPROPYLENE GLYCOL; POLYGONUM AVICULARE TOP; POLYSORBATE 20; CYCLOMETHICONE 4; DIMETHICONE/PEG-10/15 CROSSPOLYMER; SODIUM CITRATE; PEG/PPG-18/18 DIMETHICONE; ASCORBYL PALMITATE; PALMITOYL TETRAPEPTIDE-7; CAPRYLYL GLYCOL; STEARIC ACID; BUTYLENE GLYCOL; CYCLOMETHICONE 6; SODIUM BENZOATE; ALCOHOL; CYCLOTETRAPEPTIDE-24 AMINOCYCLOHEXANE CARBOXYLATE; HYDROXYTYROSOL; WINE GRAPE; ISOMALT; GREEN TEA LEAF; CITRIC ACID MONOHYDRATE; ETHYLHEXYLGLYCERIN; HYALURONATE SODIUM; LECITHIN, SOYBEAN; ARABICA COFFEE BEAN; POLYETHYLENE GLYCOL 400; TRIETHOXYSILYLETHYL POLYDIMETHYLSILOXYETHYL HEXYL DIMETHICONE; ECTOINE; CARBOMER HOMOPOLYMER, UNSPECIFIED TYPE; ALUMINUM HYDROXIDE; DIMETHICONE/POLYGLYCERIN-3 CROSSPOLYMER; CETYL PEG/PPG-10/1 DIMETHICONE (HLB 4); SORBITAN OLIVATE; BENZOIC ACID; ETHYLHEXYL PALMITATE; ASCORBIC ACID

Drug Facts

ACTIVE INGREDIENT

Active Ingredients: Zinc Oxide 8.6%, Titanium Dioxide 6.5%

Purpose: Sun Protectant

INDICATIONS AND USAGE

Uses: Broad spectrum (Sun Protection Factor 50 /SPF 50).

WARNINGS

Warning: For external use only.

Do not use on damaged or broken skin.

When using this product, avoid contact with the eyes. If contact occurs, rinse thoroughly with water.

STOP USE

Discontinue use if rash or irritation develops or lasts. If irritation persists, consult a doctor.

Keep out of reach of Children - if swallowed get medical help or contact Poison Control Center right away.

DOSAGE AND ADMINISTRATION

Directions: Adults and Children over 6 months of age: Apply generously and evenly 15 minutes before sun exposure. Reapply at least every 2 hours. Sun Protection Measures: Spending time in the sun increases your risk of skin cancer and early skin aging - to decrease this risk, regularly use a sunscreen with a Broad Spectrum SPF value of 15 or higher and take other sun protection measures including limiting time in the sun, especially from 10 a.m. - 2 p.m., and wearing long-sleeve shirts, pants, hats and sunglasses.

OTHER SAFETY INFORMATION

Sun Protection Measures: Spending time in the sun increases your risk of skin cancer and early skin aging - to decrease this risk, regularly use a sunscreen with a Broad Spectrum SPF value of 15 or higher and take other sun protection measures including limiting time in the sun, especially from 10 a.m. - 2 p.m., and wearing long-sleeve shirts, pants, hats and sunglasses.

INACTIVE INGREDIENT

Inactive Ingredients: Water (Aqua), Cyclopentasiloxane, C12-15 Alkyl Benzoate, Dimethicone, Cyclotetrasiloxane, Polyglyceryl-3 Polydimethylsiloxyethyl Dimethicone, Polysilicone-31, Glycerin, Aluminum Hydroxide, Stearic Acid, Dimethicone/PEG-10/15 Crosspolymer, Pyrus Malus (Apple) Fruit Extract, Sodium Chloride, Dipropylene Glycol, Sodium Citrate, Tocopherol, Dimethicone/Polyglycerin-3 Crosspolymer, Dimethicone / Vinyl Dimethicone Crosspolymer, Tocopheryl Acetate, PEG/PPG-18/18 Dimethicone, Polyglyceryl-4 Isostearate, Cetyl PEG/PPG-10/1 Dimethicone, Hexyl Laurate, Pentaerythrityl Tetra-di-t-butyl Hydroxyhydrocinnamate, Cetearyl Olivate, Sorbitan Olivate, Benzoic Acid, Ethylhexyl Palmitate, Silica Dimethyl Silylate, Butylene Glycol, Pentylene Glycol, Sodium Hyaluronate, Cyclohexasiloxane, PEG-8, Ascorbyl Palmitate, Ascorbic Acid, Triethoxysilylethyl Polydimethylsiloxyethyl Hexyl Dimethicone, Sodium Ferrocyanide Decahydrate, Hydroxytyrosol, Polygonum Aviculare Extract, Sodium Benzoate, Potassium Sorbate, Alcohol, Lecithin, Ectoin, Cyclotetra peptide-24 Aminocyclohexane Carboxylate, Carbomer, Polysorbate 20, Palmitoyl Tripeptide-1, Palmitoyl Tetrapeptide-7, Vitis Vinifera (Grape) Fruit Cell Extract, Isomalt, Camellia Sinensis Leaf Extract, Coffee Arabica (Coffee) Seed Extract, Citric Acid, Phenoxyethanol, Caprylyl Glycol, Ethylhexylglycerin, Hexylene Glycol, Triethoxycaprylylsilane, Iron Oxides(CI 77491, CI 77492, CI 77499)